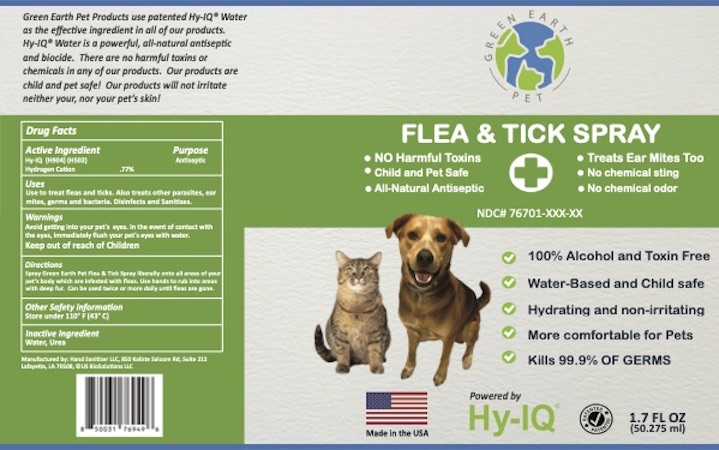 DRUG LABEL: Green Earth Pet Flea and Tick
NDC: 76701-261 | Form: SPRAY
Manufacturer: HAND SANITIZER LLC
Category: animal | Type: OTC ANIMAL DRUG LABEL
Date: 20210809

ACTIVE INGREDIENTS: HYDROGEN CATION 10 mg/1 mL
INACTIVE INGREDIENTS: WATER 940 mg/1 mL; UREA 50 mg/1 mL

Green Earth Pet Flea and Tick

Active Ingredient

Hy-IQ (H904) (H502)
Hydrogen Cation .77%

Purpose

Antiseptic

Uses

Use to treat fleas and ticks. Also treats other parasites, ear mites, germs and bacteria. Disinfects and Sanitizes.

Warnings

Avoid getting into your pet's eyes. In the event of contact with the eyes, immediately flush your pet's eyes with water.

Keep Out of Reach of Children

Directions

Spray Green Earth Pet Flea & Tick Spray liberally onto all areas of your pet's body which are infested with fleas. Use hands to rub into areas with deep fur. Can be used twice or more daily until fleas are gone.

Other Safety Information

Store under 110º F (43º C)

Inactive Ingredients

Water, Urea

Green Earth Pet Flea and Tick Spray